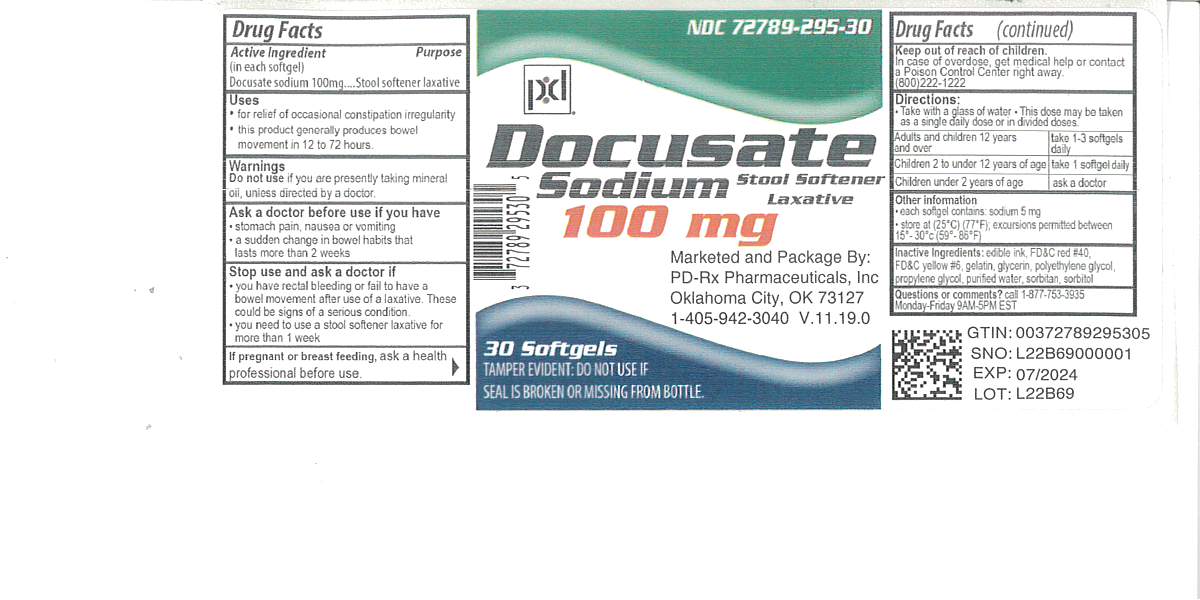 DRUG LABEL: Docusate Sodium
NDC: 72789-295 | Form: CAPSULE
Manufacturer: PD-Rx Pharmaceuticals, Inc.
Category: otc | Type: HUMAN OTC DRUG LABEL
Date: 20251001

ACTIVE INGREDIENTS: DOCUSATE SODIUM 100 mg/1 1
INACTIVE INGREDIENTS: FD&C RED NO. 40; FD&C YELLOW NO. 6; GELATIN; SORBITAN; POLYETHYLENE GLYCOL, UNSPECIFIED; PROPYLENE GLYCOL; WATER; SORBITOL; GLYCERIN; MEDIUM-CHAIN TRIGLYCERIDES

Drug Facts

Active ingredient (in each softgel)

Docusate Sodium 100 mg

Purpose

Stool softener laxative

Uses

- for relief of occasional constipation (irregularity)
- this product generally produces bowel movement in 12 to 72 hours

Warnings

Do not use

if you are presently taking mineral oil, unless told to do so by a doctor.

Ask a doctor before use if you have

- stomach pain
- nausea
- vomiting
- noticed a sudden change in bowel habits that last over 2 weeks

Stop use and ask a doctor if

- you have rectal bleeding or fail to have a bowel movement after use of a laxative. These could be a signs of a serious condition.
- you need to use a laxative for more than 1 week

If pregnant or breast-feeding,

ask a health professional before use.

Keep out of reach of children.

In case of overdose, get medical help or contact a Poison Control Center (1-800-222-1222) right away.

Directions

- take with a glass of water

adults and children 12 years and over | take 1 to 3 softgels daily. This dose may be taken as a single daily dose or in divided dose
children 2 to under 12 years of age | take 1 softgel daily
children under 2 years | ask a doctor

Other information

- each softgel contains:sodium 5 mg
- store at 25ºC (77ºF);excursions permitted between 15-30ºC (59-86ºF)

Inactive ingredients

edible ink, FD&C Red #40, FD&C Yellow #6, gelatin, glycerin, polyethylene glycol, propylene glycol, purified water sorbitan, sorbitol

Questions or comments?

Call 1-877-753-3935Monday-Friday 9AM-5PM EST

Principal Display Panel

Docusate Sodium

Stool Softener Laxative

TAMPER EVIDENT: DO NOT USE IF SEAL IS BROKEN OR MISSING FROM BOTTLE.